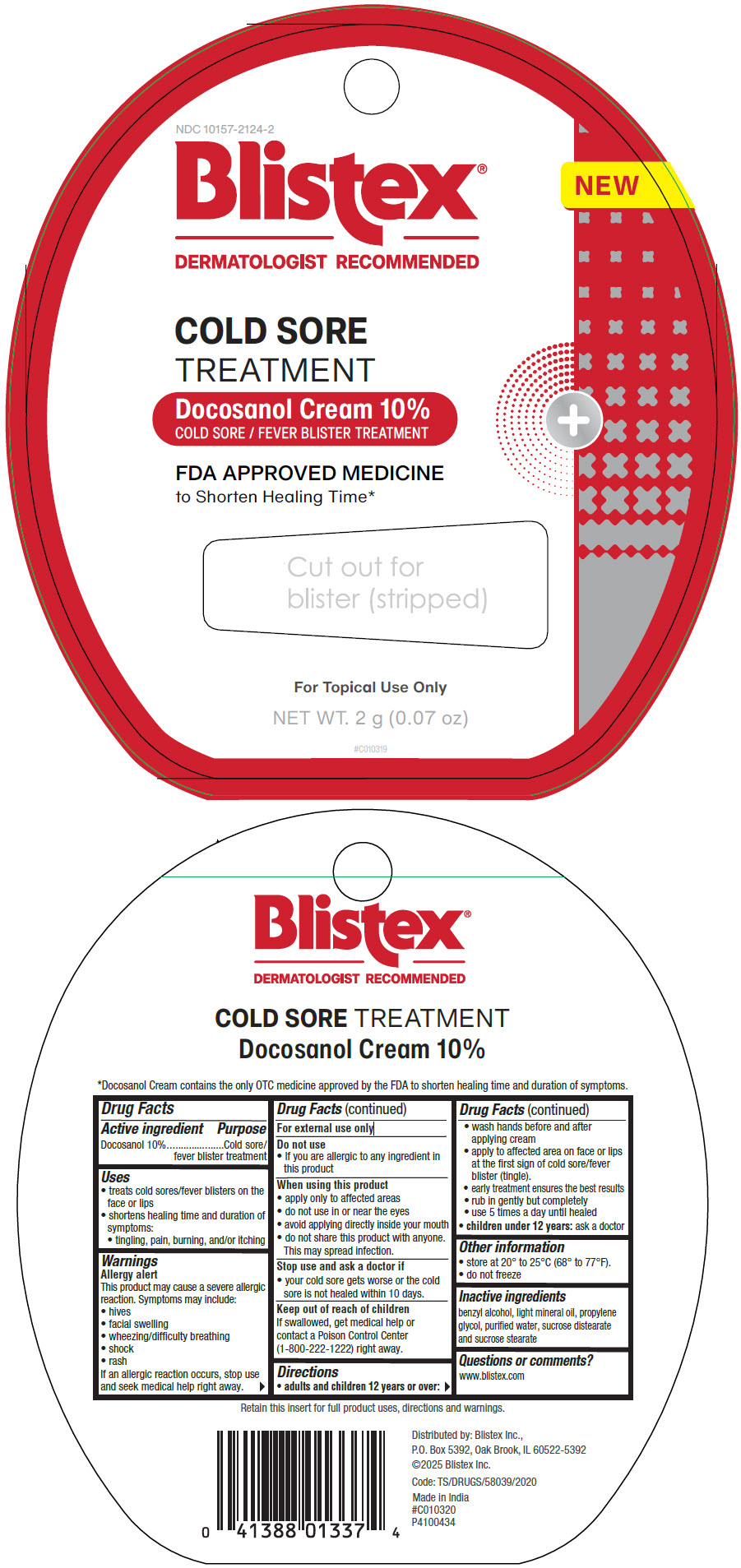 DRUG LABEL: Cold Sore Treatment Docosanol
NDC: 10157-2124 | Form: CREAM
Manufacturer: Blistex Inc.
Category: otc | Type: HUMAN OTC DRUG LABEL
Date: 20250411

ACTIVE INGREDIENTS: DOCOSANOL 100 mg/1 g
INACTIVE INGREDIENTS: BENZYL ALCOHOL; LIGHT MINERAL OIL; PROPYLENE GLYCOL; WATER; SUCROSE DISTEARATE; SUCROSE STEARATE

Cold Sore Treatment: Docosanol Cream 10%

Drug Facts

Active ingredient

Docosanol 10%

Purpose

Cold sore/ fever blister treatment

Uses

- treats cold sores/fever blisters on the face or lips
- shortens healing time and duration of symptoms:
  - tingling, pain, burning, and/or itching

Warnings

Allergy alert

This product may cause a severe allergic reaction. Symptoms may include:

- hives
- facial swelling
- wheezing/difficulty breathing
- shock
- rash

If an allergic reaction occurs, stop use and seek medical help right away.

For external use only

Do not use

- If you are allergic to any ingredient in this product

When using this product

- apply only to affected areas
- do not use in or near the eyes
- avoid applying directly inside your mouth
- do not share this product with anyone. This may spread infection.

Stop use and ask a doctor if

- your cold sore gets worse or the cold sore is not healed within 10 days.

Keep out of reach of children

If swallowed, get medical help or contact a Poison Control Center (1-800-222-1222) right away.

Directions

- adults and children 12 years or over:
  - wash hands before and after applying cream
  - apply to affected area on face or lips at the first sign of cold sore/fever blister (tingle).
  - early treatment ensures the best results
  - rub in gently but completely
  - use 5 times a day until healed
- children under 12 years: ask a doctor

Other information

- store at 20° to 25°C (68° to 77°F).
- do not freeze

Inactive ingredients

benzyl alcohol, light mineral oil, propylene glycol, purified water, sucrose distearate and sucrose stearate

Questions or comments?

www.blistex.com

Distributed by: Blistex Inc.,
P.O. Box 5392, Oak Brook, IL 60522-5392

PRINCIPAL DISPLAY PANEL - 2 g Tube Blister Pack

NDC 10157-2124-2

Blistex®

DERMATOLOGIST RECOMMENDED

NEW

COLD SORE
TREATMENT

Docosanol Cream 10%
COLD SORE / FEVER BLISTER TREATMENT

+

FDA APPROVED MEDICINE
to Shorten Healing Time*

For Topical Use Only

NET WT. 2 g (0.07 oz)

#C010319